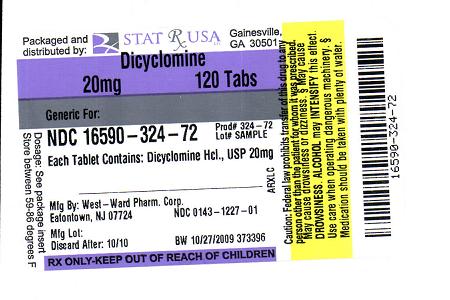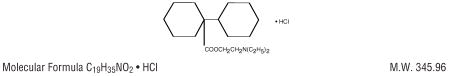 DRUG LABEL: DICYCLOMINE
NDC: 16590-324 | Form: TABLET
Manufacturer: STAT RX USA LLC
Category: prescription | Type: HUMAN PRESCRIPTION DRUG LABEL
Date: 20091027

ACTIVE INGREDIENTS: DICYCLOMINE HYDROCHLORIDE 20 mg/1 1
INACTIVE INGREDIENTS: ANHYDROUS LACTOSE; FD&C BLUE NO. 1; LACTOSE MONOHYDRATE; MAGNESIUM STEARATE; CELLULOSE, MICROCRYSTALLINE

Revised 03/04
Rx Only

DESCRIPTION

Dicyclomine hydrochloride is an antispasmodic and anticholinergic (antimuscarinic) agent available in the following form:
Each tablet, for oral administration, contains 20 mg of dicyclomine hydrochloride. They also contain the following inactive ingredients: Anhydrous Lactose, FDandC Blue No. 1 Lake, Lactose Monohydrate, Magnesium Stearate, and Microcrystalline Cellulose.
Chemically, dicyclomine hydrochloride is [bicyclohexyl]-1-carboxylic acid, 2-(diethylamino) ethylester, hydrochloride with the structural formula:

DICYCLOMINE 20MG STRUCTURE IMAGE

Dicyclomine hydrochloride occurs as a fine, white, crystalline, practically odorless powder with a bitter taste. It is soluble in water, freely soluble in alcohol and chloroform, and very slightly soluble in ether

CLINICAL PHARMACOLOGY

Dicyclomine relieves smooth muscle spasm of the gastrointestinal tract. Animal studies indicate that this action is achieved via a dual mechanism: (1) a specific anticholinergic effect (antimuscarinic) at the acetylcholine-receptor sites with approximately 1/8 the milligram potency of atropine (in vitro, guinea pig ileum); and (2) a direct effect upon smooth muscle (musculotropic) as evidenced by dicyclomine's antagonism of bradykinin- and histamine-induced spasms of the isolated guinea pig ileum. Atropine did not affect responses to these two agonists. In vivo studies in cats and dogs showed dicyclomine to be equally potent against acetylcholine (ACh)- or barium chloride (BaCl2)-induced intestinal spasm while atropine was at least 200 times more potent against effects of ACh than BaCl2. Tests for mydriatic effects in mice showed that dicyclomine was approximately 1/500 as potent as atropine; antisialagogue tests in rabbits showed dicyclomine to be 1/300 as potent as atropine.
In man, dicyclomine is rapidly absorbed after oral administration, reaching peak values within 60-90 minutes. The principal route of elimination is via the urine (79.5% of the dose). Excretion also occurs in the feces, but to a lesser extent (8.4%). Mean half-life of plasma elimination in one study was determined to be approximately 1.8 hours when plasma concentrations were measured for 9 hours after a single dose. In subsequent studies, plasma concentrations were followed for up to 24 hours after a single dose, showing a secondary phase of elimination with a somewhat longer half-life. Mean volume of distribution for a 20 mg oral dose is approximately 3.65 L/kg suggesting extensive distribution in tissues.
In controlled clinical trials involving over 100 patients who received drug, 82% of patients treated for functional bowel/irritable bowel syndrome with dicyclomine hydrochloride at initial doses of 160 mg daily (40 mg q.i.d.) demonstrated a favorable clinical response compared with 55% treated with placebo. (P less than .05). In these trials, most of the side effects were typically anticholinergic in nature (see table) and were reported by 61% of the patients.
Dicyclomine Hydrochloride
Side (40 mg q.i.d.) Placebo
Effect % %
Dry Mouth 33 5
Dizziness 29 2
Blurred Vision 27 2
Nausea 14 6
Light-Headedness 11 3
Drowsiness 9 1
Weakness 7 1
Nervousness 6 2
Nine percent (9%) of patients were discontinued from the drug because of one or more of these side effects (compared with 2% in the placebo group). In 41% of the patients with side effects, side effects disappeared or were tolerated at the 160 mg daily dose without reduction. A dose reduction from 160 mg daily to an average daily dose of 90 mg was required in 46% of the patients with side effects who then continued to experience a favorable clinical response; their side effects either disappeared or were tolerated. (See ADVERSE REACTIONS.)

INDICATIONS AND USAGE

For the treatment of functional bowel/irritable bowel syndrome.

CONTRAINDICATIONS

1. Obstructive uropathy
2. Obstructive disease of the gastrointestinal tract
3. Severe ulcerative colitis (See PRECAUTIONS)
4. Reflux esophagitis
5. Unstable cardiovascular status in acute hemorrhage
6. Glaucoma
7. Myasthenia gravis
8. Evidence of prior hypersensitivity to dicyclomine hydrochloride or other ingredients of these formulations
9. Infants less than 6 months of age (See WARNINGS and PRECAUTIONS: Information for Patients.)
10. Nursing Mothers (See WARNINGS and PRECAUTIONS: Information for Patients.)

WARNINGS

In the presence of a high environmental temperature, heat prostration can occur with drug use (fever and heat stroke due to decreased sweating). If symptoms occur, the drug should be discontinued and supportive measures instituted.
Diarrhea may be an early symptom of incomplete intestinal obstruction, especially in patients with ileostomy or colostomy. In this instance, treatment with this drug would be inappropriate and possibly harmful.
Dicyclomine hydrochloride may produce drowsiness or blurred vision. The patient should be warned not to engage in activities requiring mental alertness, such as operating a motor vehicle or other machinery or performing hazardous work while taking this drug.
Psychosis has been reported in sensitive individuals given anticholinergic drugs. CNS signs and symptoms include confusion, disorientation, short-term memory loss, hallucinations, dysarthria, ataxia, coma, euphoria, decreased anxiety, fatigue, insomnia, agitation and mannerisms, and inappropriate affect. These CNS signs and symptoms usually resolve within 12 to 24 hours after discontinuation of the drug.
DICYCLOMINE IS CONTRAINDICATED IN INFANTS LESS THAN 6 MONTHS OF AGE AND IN NURSING MOTHERS. (See CONTRAINDICATIONS and PRECAUTIONS: Nursing Mothers and Pediatric Use).
Safety and efficacy of dicyclomine hydrochloride in children have not been established.

HOW SUPPLIED

Dicyclomine Hydrochloride Tablets USP, 20 mg are supplied as blue, round, unscored tablets; embossed “WW 27” and are available in:
Bottles of 100 tablets.
Bottles of 1000 tablets.
Unit Dose Boxes of 100 tablets.
To prevent fading, avoid exposure to direct sunlight. Store at 20°-25°C (68°-77°F) [See USP Controlled Room Temperature]. Protect from light and moisture.
Dispense in a tight, light-resistant container as defined in the USP using a child-resistant closure.
Manufactured By:
West-ward Pharmaceutical Corp.
Eatontown, NJ 07724
Revised March 200

DICYCLOMINE 20MG LABEL IMAGE